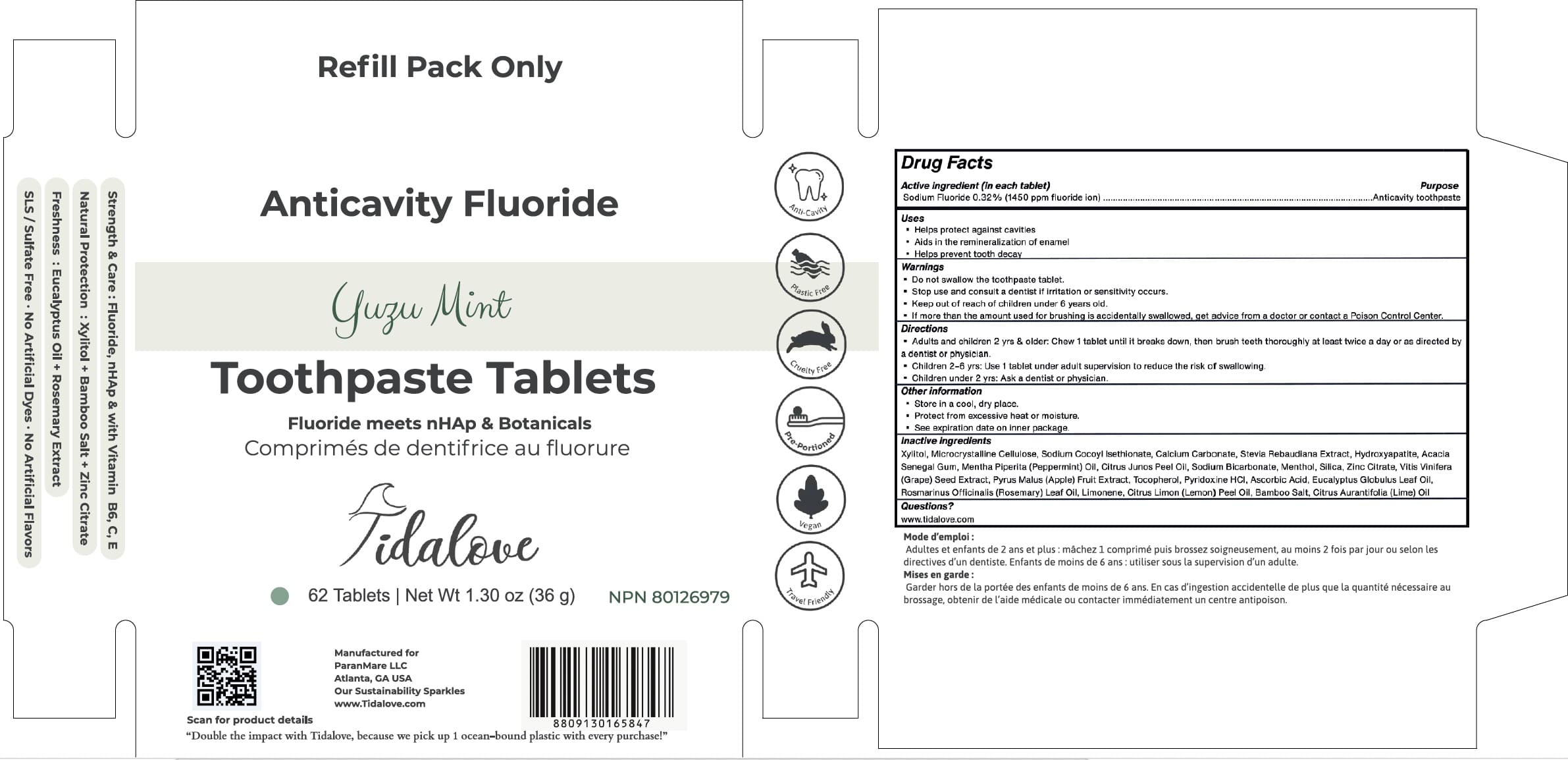 DRUG LABEL: Tidalove
NDC: 82756-221 | Form: TABLET, CHEWABLE
Manufacturer: Paranmare LLC
Category: otc | Type: HUMAN OTC DRUG LABEL
Date: 20251007

ACTIVE INGREDIENTS: SODIUM FLUORIDE 0.32 mg/1 1
INACTIVE INGREDIENTS: SODIUM CHLORIDE; STEVIOSIDE; ACACIA; LEMON OIL; TRIBASIC CALCIUM PHOSPHATE; VITIS VINIFERA SEED; APPLE; LIME OIL; SODIUM COCOYL ISETHIONATE; TOCOPHEROL; MENTHOL; CALCIUM CARBONATE; PEPPERMINT OIL; ASCORBIC ACID; LIMONENE, (+/-)-; CELLULOSE, MICROCRYSTALLINE; SODIUM BICARBONATE; PYRIDOXINE HYDROCHLORIDE; SILICON DIOXIDE; ZINC CITRATE; EUCALYPTUS OIL; ROSEMARY OIL; XYLITOL

Muyme-Paranmare Yuzu-Mint 2025

Active Ingredient(s)

Sodium Fluoride 0.32% (1450 ppm fluoride ion)

Purpose

Anti-cavity

Use

Helps protect against cavities
Aids in the remineralization of enamel
Helps prevent tooth decay

Warnings

- Do not swallow the toothpaste tablet.
  * Stop use and consult a dentist if irritation or sensitivity occurs.
  Keep out of reach of children under 6 years old.
  If more than the amount used for brushing is accidentally swallowed, get advice from a doctor or contact a Poison Control Center.

KEEP OUT OF REACH OF CHILDREN

If more than used for brushing is accidentally swallowed, get medical help or contact a Poison Control Center immediately.

Directions

- Adults and children 2 yrs & older: Chew 1 tablet until it breaks down, then brush teeth thoroughly at least twice a day or as directed by a dentist or physician.
  Children 2-6 yrs: Use 1 tablet under adult supervision to reduce the risk of swallowing.
  Children under 2 yrs: Ask a dentist or physician.

Other information

Store in a cool, dry place.
Protect from excessive heat or moisture.
See expiration date on inner package.

Inactive ingredients

Xylitol, Microcrystalline Cellulose, Sodium Cocoyl Isethionate, Calcium Carbonate, Stevia Rebaudiana Extract, Hydroxyapatite, Acacia Senegal Gum, Mentha Piperita (Peppermint) Oil, Citrus Junos Peel Oil, Sodium Bicarbonate, Menthol, Silica, Zinc Citrate, Vitis Vinifera (Grape) Seed Extract, Pyrus Malus (Apple) Fruit Extract, Tocopherol, Pyridoxine HCI, Ascorbic Acid, Eucalyptus Globulus Leaf Oil, Rosmarinus Officinalis (Rosemary) Leaf Oil, Limonene, Citrus Limon (Lemon) Peel Oil, Bamboo Salt, Citrus Aurantifolia (Lime) Oil

QUESTIONS

www.tidalove.com